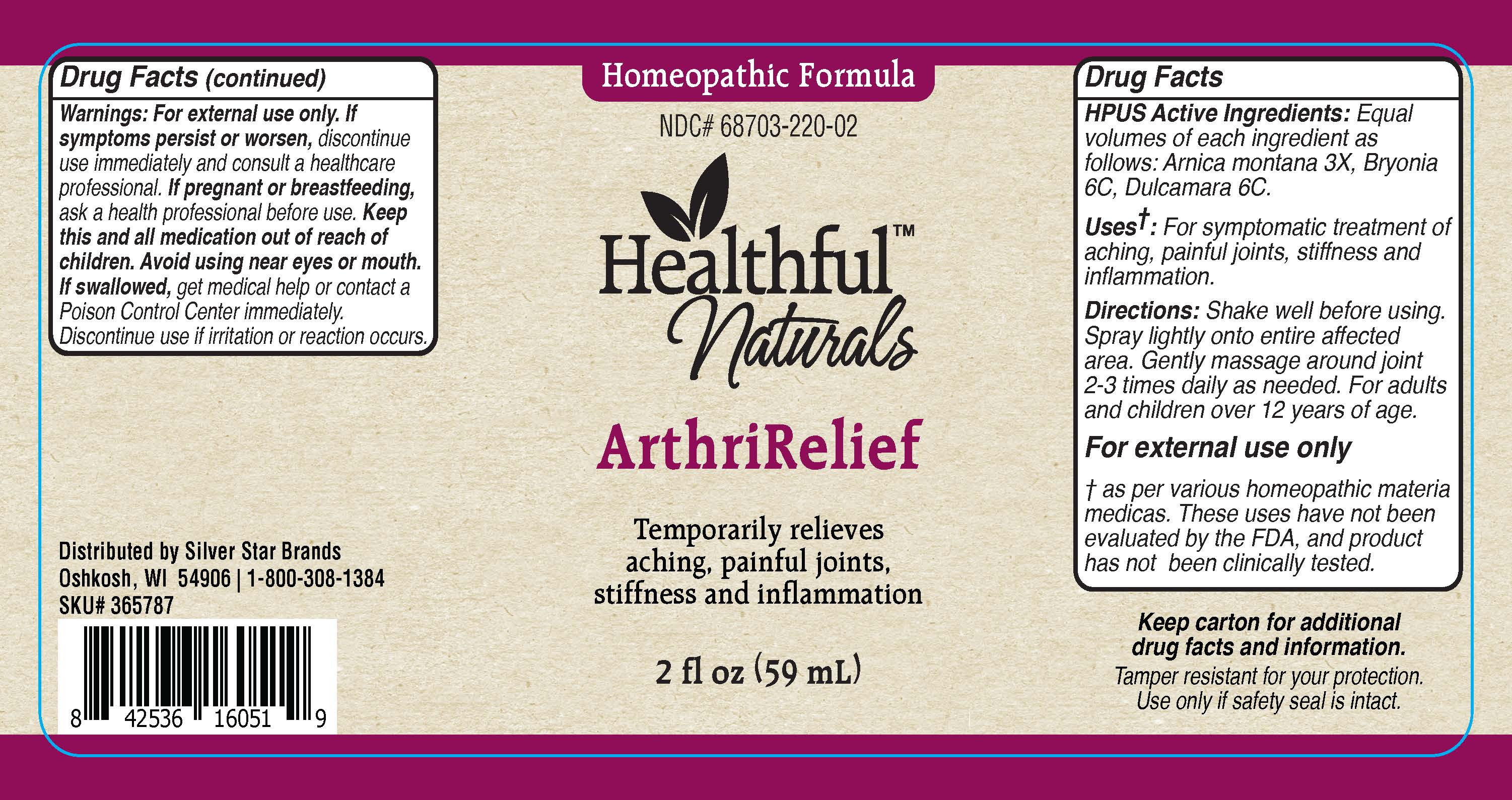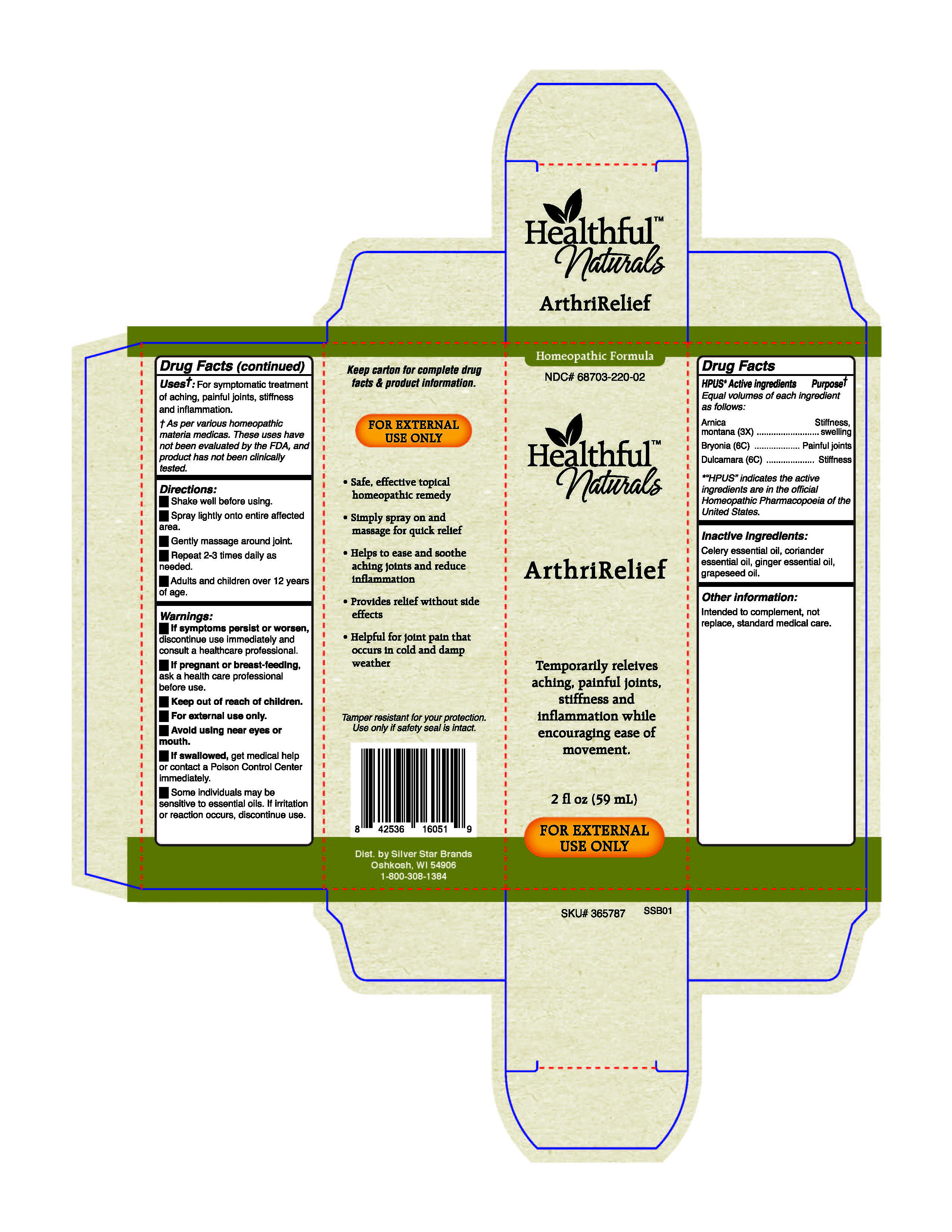 DRUG LABEL: ArthriRelief
NDC: 68703-220 | Form: SPRAY
Manufacturer: Silver Star Brands
Category: homeopathic | Type: HUMAN OTC DRUG LABEL
Date: 20190228

ACTIVE INGREDIENTS: BRYONIA ALBA ROOT 6 [hp_C]/59 mL; ARNICA MONTANA 3 [hp_X]/59 mL; SOLANUM DULCAMARA FLOWER 6 [hp_C]/59 mL
INACTIVE INGREDIENTS: CELERY SEED OIL; GINGER OIL; CORIANDER OIL; GRAPE SEED OIL

Healthful™ Naturals ArthriRelief - 59 ml

HPUS* Active ingredients - Equal volumes of each ingredient as follows:

Arnica montana (3X), Bryonia (6C), Dulcamara (6C).

*"HPUS" indicates the active ingredients are in the official Homeopathic Pharmacopoeia of the United States.

Uses+

Uses+: For symptomatic treatment of aching, painful joints, stiffness and inflammation.

+As per various homeopathic materia medicas. These uses have not been evaluated by the FDA, and product has not been clinically tested.

Warnings

Warnings: If symptoms persist or worsen, discontinue use immediately and consult a healthcare professional.

If pregnant or breast-feeding, ask a healthcare professional before use.

Keep out of reach of children.

For external use only.

Avoid using near eyes or mouth.

If swallowed, get medical help or contact a Poison Control Center immediately.

Some individuals may be sensitive to essential oils. If irritation or reaction occurs, discontinue use.

Directions

Shake well before using.

Spray lightly onto entire affected area.

Gently massage around joint.

Repeat 2-3 times daily as needed.

Adults and children over 12 years of age.

Other information:

Intended to complement, not replace, standard medical care.

Tamper resistant for your protection. Use only if safety seal is intact.

Inactive ingredients

Inactive ingredients: Celery essential oil, coriander essential oil, ginger essential oil, grapeseed oil.

Keep out of reach of children.

PREGNANCY OR BREAST FEEDING

If pregnant or breastfeeding, ask a healthcare professional before use.

HPUS* Active ingredients Purpose+

Equal volumes of each ingredient as follows:

Arnica montana (3X)......................................Stiffness, swelling

Bryonia (6C)...................................................Painful joints

Dulcamara (6C).............................................Stiffness